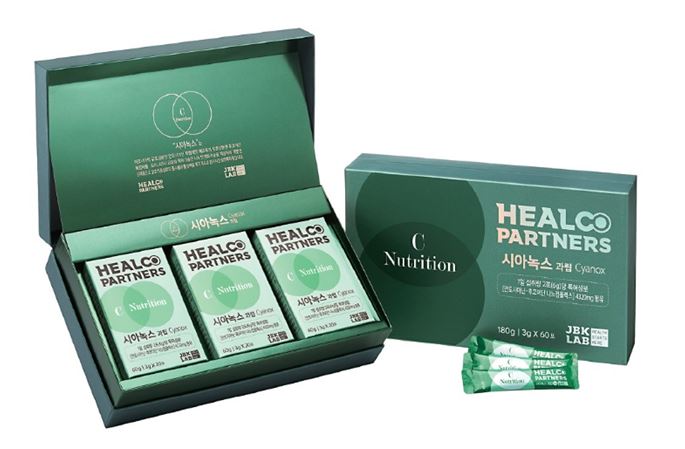 DRUG LABEL: CYANOX
NDC: 72173-0001 | Form: GRANULE
Manufacturer: JBKLAB Co., Ltd
Category: otc | Type: HUMAN OTC DRUG LABEL
Date: 20180313

ACTIVE INGREDIENTS: CHICORY LEAF 90 g/100 g
INACTIVE INGREDIENTS: ARONIA MELANOCARPA FRUIT

ACTIVE INGREDIENT

chicory extract powder, aronia extract powder, kelp extract powder

INACTIVE INGREDIENT

Natural raspberry flavor, enzyme treated stevia

PURPOSE

• Application for a patent : Adjuvants and anticancer immuno-therapeutic agents comprising anthoyanin- fucoidan complex
• Registration of a patent : Anthocyanin via Charge Complex with Anionic Polysaccharide Having Improved Stability, Composition Containing the Same, and Method for Preparing the Same

WARNINGS

• Application for a patent : Adjuvants and anticancer immuno-therapeutic agents comprising anthoyanin- fucoidan complex
• Registration of a patent : Anthocyanin via Charge Complex with Anionic Polysaccharide Having Improved Stability, Composition Containing the Same, and Method for Preparing the Same

Keep out of reach of children.

INDICATIONS AND USAGE

Take 1 stick once a time, and twice a day

DOSAGE AND ADMINISTRATION

for oral use only